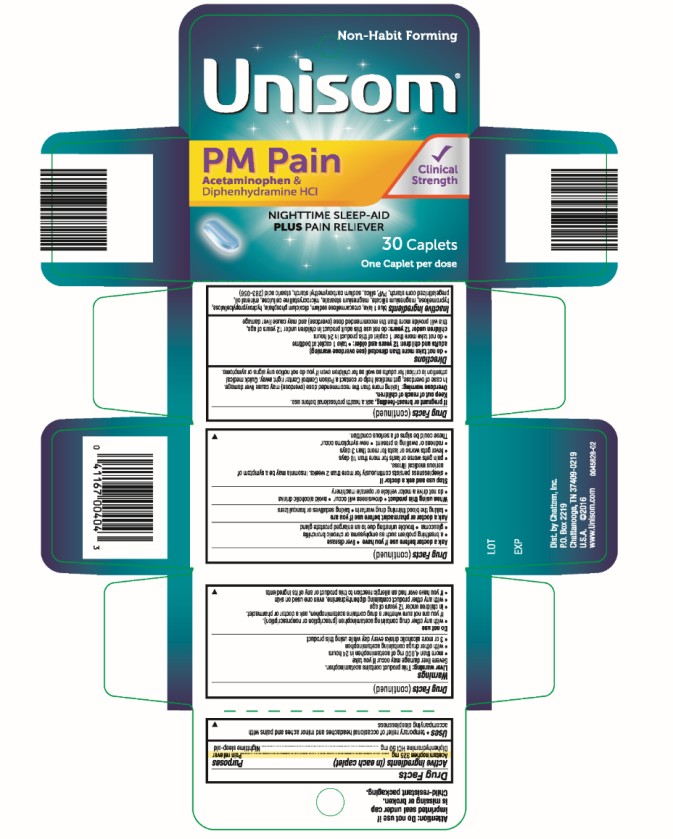 DRUG LABEL: Unisom PM Pain Nighttime Sleep Aid and Pain Reliever
NDC: 41167-0040 | Form: TABLET, FILM COATED
Manufacturer: Chattem, Inc.
Category: otc | Type: HUMAN OTC DRUG LABEL
Date: 20260114

ACTIVE INGREDIENTS: ACETAMINOPHEN 325 mg/1 1; DIPHENHYDRAMINE HYDROCHLORIDE 50 mg/1 1
INACTIVE INGREDIENTS: FD&C BLUE NO. 1; CROSCARMELLOSE SODIUM; DIBASIC CALCIUM PHOSPHATE DIHYDRATE; HYDROXYPROPYL CELLULOSE, UNSPECIFIED; HYPROMELLOSES; MAGNESIUM SILICATE; MAGNESIUM STEARATE; CELLULOSE, MICROCRYSTALLINE; LIGHT MINERAL OIL; STARCH, CORN; POVIDONE K30; SILICON DIOXIDE; SODIUM STARCH GLYCOLATE TYPE A POTATO; STEARIC ACID

Unisom PM Pain Nighttime Sleep-Aid and Pain Reliever

Drug Facts

Active ingredients

(in each caplet)

Acetaminophen 325 mg

Purposes

Pain reliever

Active ingredients

(in each caplet)

Diphenhydramine HCl 50 mg

Purposes

Nighttime sleep-aid

Uses

- for the temporary relief of occasional headaches and minor aches and pains with accompanying sleeplessness

Warnings

Liver warning:

This product contains acetaminophen. Severe liver damage may occur if you take

- more than 4,000 mg of acetaminophen in 24 hours
- with other drugs containing acetaminophen
- 3 or more alcoholic drinks every day while using this product

Do not use

- with any other drug containing acetaminophen (prescription or nonprescription). If you are not sure whether a drug contains acetaminophen, ask a doctor or pharmacist.
- in children under 12 years of age
- with any other product containing diphenhydramine, even one used on skin
- if you have ever had an allergic reaction to this product or any of its ingredients

Ask a doctor before use if

you have

- liver disease
- a breathing problem such as emphysema or chronic bronchitis
- trouble urinating due to an enlarged prostate gland
- glaucoma

Ask a doctor or pharmacist before use if you are

- taking the blood thinning drug warfarin
- taking sedatives or tranquilizers

When using this product

- drowsiness will occur
- avoid alcoholic drinks
- do not drive a motor vehicle or operate machinery

Stop use and ask a doctor if

- sleeplessness persists continuously for more than 2 weeks. Insomnia may be a symptom of serious medical illness.
- pain gets worse or lasts for more than 10 days
- fever gets worse or lasts for more than 3 days
- redness or swelling is present
- new symptoms occur

These could be signs of a serious condition.

If pregnant or breast-feeding,

ask a health professional before use.

Overdose warning:

Taking more than the recommended dose (overdose) may cause liver damage. In case of overdose, get medical help or contact a Poison Control Center right away. Quick medical attention is critical for adults as well as for children even if you do not notice any signs or symptoms.

Directions

• do not take more than directed (see overdose warning)

adults and children 12 years and older: • take 1 caplet at bedtime

• do not take more than 1 caplet of this product in 24 hours

children under 12 years: do not use this adult product in children under 12 years of age, this will provide more than the recommended dose (overdose) and may cause liver damage

Inactive ingredients

blue 1 lake, croscarmellose sodium, dicalcium phosphate, hydroxypropylcellulose, hypromellose, magnesium silicate, magnesium stearate, microcrystalline cellulose, mineral oil, pregelatinized corn starch, PVP, silica, sodium carboxymethyl starch, stearic acid (283-056)

PRINCIPAL DISPLAY PANEL

Unisom®
PM PAIN
SLEEPCAPSTM
30 Caplets